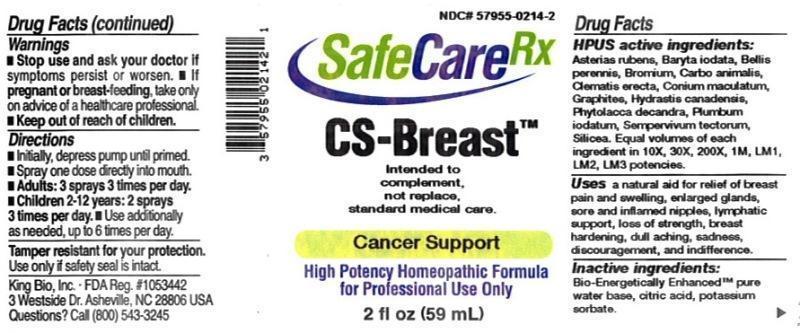 DRUG LABEL: CS Breast
NDC: 57955-0214 | Form: LIQUID
Manufacturer: King Bio Inc.
Category: homeopathic | Type: HUMAN OTC DRUG LABEL
Date: 20150602

ACTIVE INGREDIENTS: ASTERIAS RUBENS 10 [hp_X]/59 mL; BARIUM IODIDE 10 [hp_X]/59 mL; BELLIS PERENNIS 10 [hp_X]/59 mL; BROMINE 10 [hp_X]/59 mL; CARBO ANIMALIS 10 [hp_X]/59 mL; CONIUM MACULATUM FLOWERING TOP 10 [hp_X]/59 mL; GRAPHITE 10 [hp_X]/59 mL; GOLDENSEAL 10 [hp_X]/59 mL; PHYTOLACCA AMERICANA ROOT 10 [hp_X]/59 mL; LEAD IODIDE 10 [hp_X]/59 mL; SEMPERVIVUM TECTORUM LEAF 10 [hp_X]/59 mL; SILICON DIOXIDE 10 [hp_X]/59 mL
INACTIVE INGREDIENTS: WATER; ANHYDROUS CITRIC ACID; POTASSIUM SORBATE

CS Breast™

ACTIVE INGREDIENT

Drug Facts__________________________________________________________________________________________________________

HPUS active ingredients: Asterias rubens, Baryta lodata, Bellis perennis, Bromium, Carbo animalis, Clematis erecta, Conium maculatum, Graphites, Hydrastis canadensis, Phytolacca decandra, Plumbum iodatum, Sempervivum tectorum, Silicea. Equal volumes of each ingredient in 10X, 30X, 200X, 1M, LM1, LM2, LM3 potencies.

INDICATIONS AND USAGE

Uses a natural aid for relief of breast pain and swelling, enlarged glands, sore and inflamed nipples, lymphatic support, loss of strength, breast hardening, dull aching, sadness, discouragement, and indifference.

Inactive Ingredients:

Bio-Energetically Enhanced™ pure water, citric acid and potassium sorbate.

Warnings

- Stop use and ask your doctor if symptoms persist or worsen.
- If pregnant or breast-feeding, take only on advice of a healthcare professional.

- Keep out of reach of children.

Directions

- Initially, depress pump until primed.
- Spray one dose directly into mouth.
- Adults: 3 sprays 3 times per day.
- Children 2-12: 2 sprays 3 times per day.
- Use additionally as needed, up to 6 times per day.

OTHER SAFETY INFORMATION

Tamper resistant for your protection. Use only if safety seal is intact. Intended to complement, not replace, standard medical care.

PURPOSE

Uses a natural aid for relief of:

- breast pain and swelling
- enlarged glands
- sore and inflamed nipples
- lymphatic support
- loss of strength
- breast harding
- dull aching
- sadness
- discouragement
- indifference